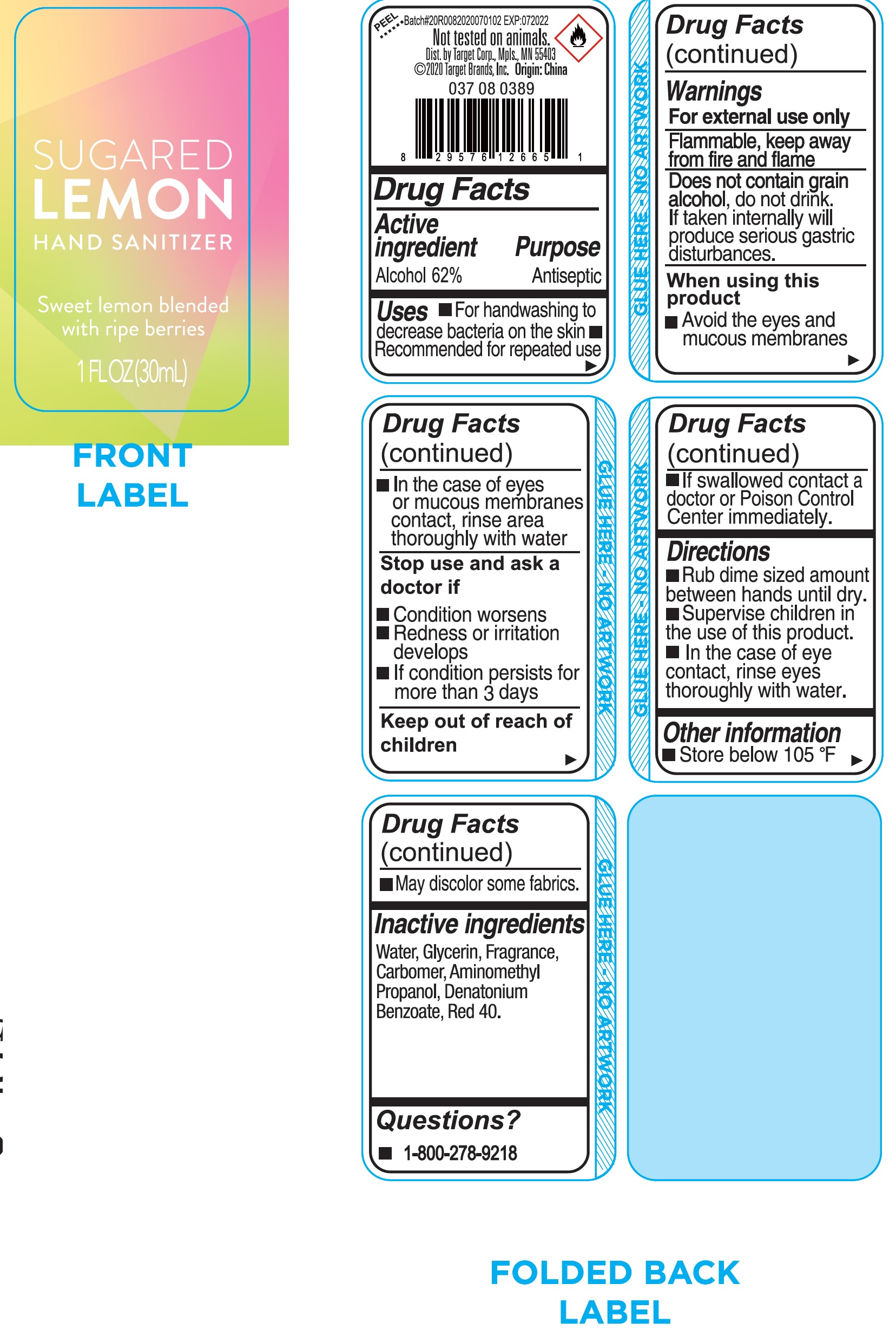 DRUG LABEL: SUGARED LEMON HAND SANITIZER
NDC: 11673-783 | Form: GEL
Manufacturer: Target Corporation
Category: otc | Type: HUMAN OTC DRUG LABEL
Date: 20231026

ACTIVE INGREDIENTS: ALCOHOL 0.62 mL/1 mL
INACTIVE INGREDIENTS: WATER; GLYCERIN; CARBOMER HOMOPOLYMER, UNSPECIFIED TYPE; AMINOMETHYLPROPANOL; DENATONIUM BENZOATE; FD&C RED NO. 40

SUGARED LEMON HAND SANITIZER

Active ingredient

Alcohol 62%

Purpose

Antiseptic

Uses

- For handwashing to decrease bacteria on the skin
- Recommended for repeated use

Warnings

For external use only

Flammable, keep away from fire and flame

do not drink. If taken internally will produce serious gastric disturbance. Does not contain grain alcohol,

When using this product

- Avoid the eyes and mucous membranes
- In the case of eyes or mucous membranes contact, rinse area thoroughly with water

Stop use and ask a doctor if

- Condition worsens
- Redness or irritation develops
- If condition persists for more than 3 days

Keep out of reach of children

If swallowed contact a doctor or Poison Control Center immediately.

Directions

- Rub dime sized amount between hands until dry.
- Supervise children in the use of this product.
- In the case of eye contact, rinse eyes thoroughly with water.

Other information

- Store below 105 °F
- may discolor some fabrics.

Inactive ingredients

Water, Glycerin, Fragrance, Carbomer, Aminomethyl Propanol, Denatonium Benzoate, Red 40.

Questions?

- 1-800-278-9218